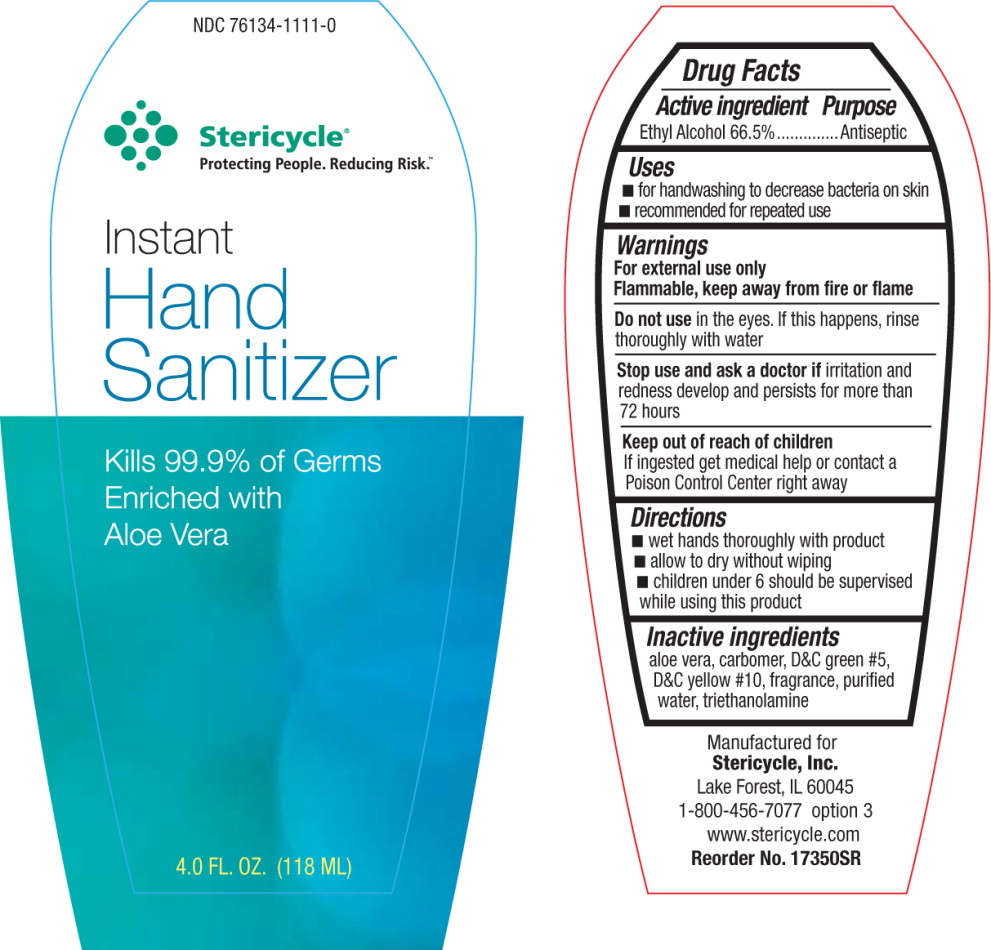 DRUG LABEL: Instant Hand Sanitizer
NDC: 76134-1111 | Form: GEL
Manufacturer: Stericycle, Inc.
Category: otc | Type: HUMAN OTC DRUG LABEL
Date: 20110518

ACTIVE INGREDIENTS: alcohol 665 mL/1 L
INACTIVE INGREDIENTS: aloe; water; trolamine

Drug Facts

Active Ingredient

Ethyl Alcohol 66.5%

Purpose

Antiseptic

Uses

- for handwashing to decrease bacteria on skin
- recommended for repeated use

Warnings

For external use only

Flammable, keep away from fire or flame

Do not use in the eyes. If this happens, rinse thoroughly with water

Stop use and ask a doctor if irritation and redness develop and persists for more than 72 hours

Keep out of reach of children

If ingested get medical help or contact a Poison Control Center right away

Directions

- wet hands thoroughly with product
- allow to dry without wiping
- children under 6 should be supervised while using this product

Inactive ingredients

aloe vera, carbomer, D&C green #5, D&C yellow #10, fragrance, purified water, triethanolamine

Manufactured for

Stericycle, Inc.
Lake Forest, IL 60045
1-800-456-7077 option 3
www.stericycle.com
Reorder No. 17350SR

PRINCIPAL DISPLAY PANEL

NDC 76134-1111-0

Stericycle

Protecting People. Reducing Risk.

Instant

Hand

Sanitizer

Kills 99.9% of Germs

Enriched with

Aloe Vera

4 FL. OZ. (118 ML)